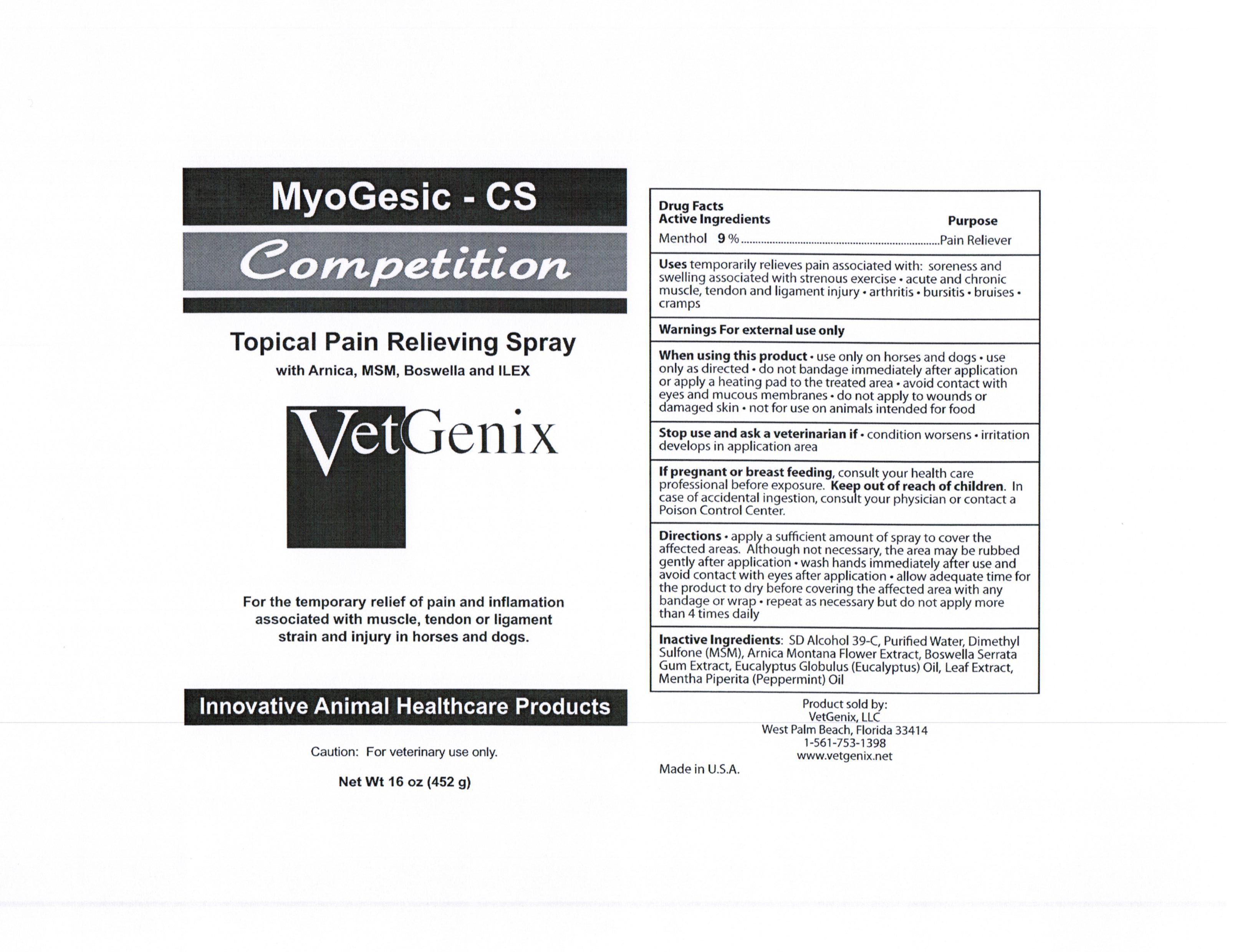 DRUG LABEL: MYOGESIC-CS 
NDC: 61600-054 | Form: SPRAY
Manufacturer: VETGENIX
Category: animal | Type: OTC ANIMAL DRUG LABEL
Date: 20111003

ACTIVE INGREDIENTS: MENTHOL 9 g/100 g

DRUG FACTS

ACTIVE INGREDIENT

Menthol 9.0% Pain Reliever

PURPOSE

temporarily relieves pain associated with soreness and swelling with strenuous exercise

acute and chronic muscle, tendon and ligament injury

arthritis

bursitis

bruises

cramps

WARNINGS

FOR EXTERNAL USE ONLY

stop use and ask veterinarian if:

condition worsens

irritation develops in application areas

Keep out of reach of children

In case of accidental ingestion, consult your physician or contact a Poison Control Center

WHEN USING THIS PRODUCT:

use only on horses and dogs

use only as directed

do not bandage immediately after application or apply heating pad to the treated area

avoid contact with eyes and mucous membranes

do not apply to wounds or damaged skin

not for use on animals intended for food

DIRECTIONS:

apply a sufficient amount of spray to cover the affected areas

although not necessary, the area may be rubbed gently after application

wash hands immediately after use and avoid contact with eyes after application

allow adequate time for the product to dry before covering the affected area with any bandage or wrap

repeat as necessary but do not apply more than 4 times daily

INACTIVE INGREDIENT

Arnica Montana Extract, Boswella Serata Extract, Symphytum Officinalis Extract, Eucalyptus Globulus Leaf Oil, Ilex Paraguariensis Extract, Dimethyl Sulfone, Mentha Piperita Leaf Oil, Purified Water, SD Alcohol 39C

Package/Label Principal Display Panel

Bottle Label

PREGNANCY OR BREAST FEEDING

If pregnant or breast feeding, consult your health care professional before exposure.